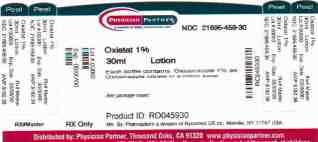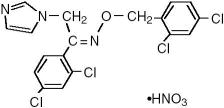 DRUG LABEL: Oxistat
NDC: 21695-459 | Form: LOTION
Manufacturer: Rebel Distributors Corp.
Category: prescription | Type: HUMAN PRESCRIPTION DRUG LABEL
Date: 20091030

ACTIVE INGREDIENTS: oxiconazole nitrate 30 mg/1 g
INACTIVE INGREDIENTS: water; petrolatum; stearyl alcohol; propylene glycol; polysorbate 60; cetyl alcohol; benzoic acid

OXISTAT® (oxiconazole nitrate cream) Cream, 1%*
OXISTAT® (oxiconazole nitrate lotion) Lotion, 1%*

*Potency expressed as oxiconazole

Rx Only

FOR TOPICAL DERMATOLOGIC USE ONLY—
NOT FOR OPHTHALMIC OR INTRAVAGINAL USE

DESCRIPTION

OXISTAT® (oxiconazole nitrate cream) Cream, 1% and OXISTAT® (oxiconazole nitrate lotion) Lotion, 1% formulations contain the antifungal active compound oxiconazole nitrate. Both formulations are for topical dermatologic use only.

Chemically, oxiconazole nitrate is 2',4'-dichloro-2-imidazol-1-ylacetophenone (Z)-[0-(2,4-dichlorobenzyl)oxime], mononitrate. The compound has the molecular formula C18H13ON3CI4·HNO3, a molecular weight of 492.15, and the following structural formula:

Oxiconazole nitrate is a nearly white crystalline powder, soluble in methanol; sparingly soluble in ethanol, chloroform, and acetone; and very slightly soluble in water.

OXISTAT® Cream contains 10 mg of oxiconazole per gram of cream in a white to off-white, opaque cream base of purified water USP, white petrolatum USP, stearyl alcohol NF, propylene glycol USP, polysorbate 60 NF, cetyl alcohol NF, and benzoic acid USP 0.2% as a preservative.

OXISTAT® Lotion contains 10 mg of oxiconazole per gram of lotion in a white to off-white, opaque lotion base of purified water USP, white petrolatum USP, stearyl alcohol NF, propylene glycol USP, polysorbate 60 NF, cetyl alcohol NF, and benzoic acid USP 0.2% as a preservative.

CLINICAL PHARMACOLOGY

PHARMACOKINETICS

Pharmacokinetics: The penetration of oxiconazole nitrate into different layers of the skin was assessed using an in vitro permeation technique with human skin. Five hours after application of 2.5 mg/cm^2 of oxiconazole nitrate cream onto human skin, the concentration of oxiconazole nitrate was demonstrated to be 16.2 μmol in the epidermis, 3.64 μmol in the upper corium, and 1.29 μmol in the deeper corium. Systemic absorption of oxiconazole nitrate is low. Using radiolabeled drug, less than 0.3% of the applied dose of oxiconazole nitrate was recovered in the urine of volunteer subjects up to 5 days after application of the cream formulation.

Neither in vitro nor in vivo studies have been conducted to establish relative activity between the lotion and cream formulations.

Microbiology: Oxiconazole nitrate is an imidazole derivative whose antifungal activity is derived primarily from the inhibition of ergosterol biosynthesis, which is critical for cellular membrane integrity. It has in vitro activity against a wide range of pathogenic fungi.

Oxiconazole has been shown to be active against most strains of the following organisms both in vitro and in clinical infections at indicated body sites (see INDICATIONS AND USAGE):

Epidermophyton floccosum
Trichophyton mentagrophytes
Trichophyton rubrum
Malassezia furfur

The following in vitro data are available; however, their clinical significance is unknown. Oxiconazole exhibits satisfactory in vitro minimum inhibitory concentrations (MICs) against most strains of the following organisms; however, the safety and efficacy of oxiconazole in treating clinical infections due to these organisms have not been established in adequate and well-controlled clinical trials:

Candida albicans
Microsporum audouini
Microsporum canis
Microsporum gypseum
Trichophyton tonsurans
Trichophyton violaceum

INDICATIONS AND USAGE

OXISTAT® Cream and Lotion are indicated for the topical treatment of the following dermal infections: tinea pedis, tinea cruris, and tinea corporis due to Trichophyton rubrum, Trichophyton mentagrophytes, or Epidermophyton floccosum. OXISTAT® Cream is indicated for the topical treatment of tinea (pityriasis) versicolor due to Malassezia furfur (see DOSAGE AND ADMINISTRATION and CLINICAL STUDIES).

OXISTAT® Cream may be used in pediatric patients for tinea corporis, tinea cruris, tinea pedis, and tinea (pityriasis) versicolor; however, these indications for which OXISTAT® Cream has been shown to be effective rarely occur in children below the age of 12.

CONTRAINDICATIONS

OXISTAT® Cream and Lotion are contraindicated in individuals who have shown hypersensitivity to any of their components.

WARNINGS

OXISTAT® (oxiconazole nitrate cream)Cream, 1% and OXISTAT® (oxiconazole nitrate lotion) Lotion, 1% are not for ophthalmic or intravaginal use.

PRECAUTIONS

GENERAL PRECAUTIONS

General: OXISTAT® Cream and Lotion are for external dermal use only. Avoid introduction of OXISTAT® Cream or Lotion into the eyes or vagina. If a reaction suggesting sensitivity or chemical irritation should occur with the use of OXISTAT® Cream or Lotion, treatment should be discontinued and appropriate therapy instituted. If signs of epidermal irritation should occur, the drug should be discontinued.

PATIENT COUNSELING INFORMATION

Information for Patients: The patient should be instructed to:

1. Use OXISTAT® as directed by the physician. The hands should be washed after applying the medication to the affected area(s). Avoid contact with the eyes, nose, mouth, and other mucous membranes. OXISTAT® is for external use only.
2. Use the medication for the full treatment time recommended by the physician, even though symptoms may have improved. Notify the physician if there is no improvement after 2 to 4 weeks, or sooner if the condition worsens (see below).
3. Inform the physician if the area of application shows signs of increased irritation, itching, burning, blistering, swelling, or oozing.
4. Avoid the use of occlusive dressings unless otherwise directed by the physician.
5. Do not use this medication for any disorder other than that for which it was prescribed.

DRUG INTERACTIONS

Drug Interactions: Potential drug interactions between OXISTAT® and other drugs have not been systematically evaluated.

CARCINOGENESIS AND MUTAGENESIS AND IMPAIRMENT OF FERTILITY

Carcinogenesis, Mutagenesis, Impairment of Fertility: Although no long-term studies in animals have been performed to evaluate carcinogenic potential, no evidence of mutagenic effect was found in 2 mutation assays (Ames test and Chinese hamster V79 in vitro cell mutation assay) or in 2 cytogenetic assays (human peripheral blood lymphocyte in vitro chromosome aberration assay and in vivo micronucleus assay in mice).

Reproductive studies revealed no impairment of fertility in rats at oral doses of 3 mg/kg/day in females (1 time the human dose based on mg/m^2) and 15 mg/kg/day in males (4 times the human dose based on mg/m^2). However, at doses above this level, the following effects were observed: a reduction in the fertility parameters of males and females, a reduction in the number of sperm in vaginal smears, extended estrous cycle, and a decrease in mating frequency.

TERATOGENIC EFFECTS

Pregnancy: Teratogenic Effects: Pregnancy Category B. Reproduction studies have been performed in rabbits, rats, and mice at oral doses up to 100, 150, and 200 mg/kg/day (57, 40, and 27 times the human dose based on mg/m^2), respectively, and revealed no evidence of harm to the fetus due to oxiconazole nitrate. There are, however, no adequate and well-controlled studies in pregnant women. Because animal reproduction studies are not always predictive of human response, this drug should be used during pregnancy only if clearly needed.

NURSING MOTHERS

Nursing Mothers: Because oxiconazole is excreted in human milk, caution should be exercised when the drug is administered to a nursing woman.

PEDIATRIC USE

Pediatric Use: OXISTAT® Cream may be used in pediatric patients for tinea corporis, tinea cruris, tinea pedis, and tinea (pityriasis) versicolor; however, these indications for which OXISTAT® Cream has been shown to be effective rarely occur in children below the age of 12.

GERIATRIC USE

Geriatric Use: A limited number of patients at or above 60 years of age (n ~ 396) have been treated with OXISTAT® Cream in US and non-US clinical trials, and a limited number (n = 43) have been treated with OXISTAT® Lotion in US clinical trials. The number of patients is too small to permit separate analysis of efficacy and safety. No adverse events were reported with OXISTAT® Lotion in geriatric patients, and the adverse reactions reported with OXISTAT® Cream in this population were similar to those reported by younger patients. Based on available data, no adjustment of dosage of OXISTAT® Cream and Lotion in geriatric patients is warranted.

ADVERSE REACTIONS

During clinical trials, of 955 patients treated with oxiconazole nitrate cream, 1%, 41 (4.3%) reported adverse reactions thought to be related to drug therapy. These reactions included pruritus (1.6%); burning (1.4%); irritation and allergic contact dermatitis (0.4% each); folliculitis (0.3%); erythema (0.2%); and papules, fissure, maceration, rash, stinging, and nodules (0.1% each).

In a controlled, multicenter clinical trial of 269 patients treated with oxiconazole nitrate lotion, 1%, 7 (2.6%) reported adverse reactions thought to be related to drug therapy. These reactions included burning and stinging (0.7% each) and pruritus, scaling, tingling, pain, and dyshidrotic eczema (0.4% each).

OVERDOSAGE

When 5% oxiconazole cream (5 times the concentration of the marketed product) was applied at a rate of 1 g/kg to approximately 10% of body surface area of a group of 40 male and female rats for 35 days, 3 deaths and severe dermal inflammation were reported. No overdoses in humans have been reported with use of oxiconazole nitrate cream or lotion.

DOSAGE AND ADMINISTRATION

OXISTAT® Cream or Lotion should be applied to affected and immediately surrounding areas once to twice daily in patients with tinea pedis, tinea corporis, or tinea cruris. OXISTAT® Cream should be applied once daily in the treatment of tinea (pityriasis) versicolor. Tinea corporis, tinea cruris, and tinea (pityriasis) versicolor should be treated for 2 weeks and tinea pedis for 1 month to reduce the possibility of recurrence. If a patient shows no clinical improvement after the treatment period, the diagnosis should be reviewed.

Note: Tinea (pityriasis) versicolor may give rise to hyperpigmented or hypopigmented patches on the trunk that may extend to the neck, arms, and upper thighs. Treatment of the infection may not immediately result in restoration of pigment to the affected sites. Normalization of pigment following successful therapy is variable and may take months, depending on individual skin type and incidental sun exposure. Although tinea (pityriasis) versicolor is not contagious, it may recur because the organism that causes the disease is part of the normal skin flora.

CLINICAL STUDIES

The following definitions were applied to the clinical and microbiological outcomes in patients enrolled in the clinical trials that form the basis for the approvals of OXISTAT® Lotion and OXISTAT® Cream.

Definitions:

1. Mycological Cure: No evidence (culture and KOH preparation) of the baseline (original) pathogen in a specimen from the affected area taken at the 2-week post-treatment visit (for tinea [pityriasis] versicolor, mycological cure was limited to KOH only).
2. Treatment Success: Both a global evaluation of 90% clinical improvement and a microbiologic eradication (see above) at the 2-week post-treatment visit.

Tinea Pedis: THERE ARE NO HEAD-TO-HEAD COMPARISON TRIALS OF THE OXISTAT® CREAM AND LOTION FORMULATIONS IN THE TREATMENT OF TINEA PEDIS.

Lotion Formulation: The clinical trial for the lotion formulation line extension involved 332 evaluable patients with clinically and microbiologically established tinea pedis. Of these evaluable patients, 64% were diagnosed with hyperkeratotic plantar tinea pedis and 28% with interdigital tinea pedis. Seventy-seven percent (77%) had disease secondary to infection with Trichophyton rubrum, 18% had disease secondary to infection with Trichophyton mentagrophytes, and 4% had disease secondary to infection with Epidermophyton floccosum.

The results of this clinical trial at the 2-week post-treatment follow-up visit are shown in the following table:

 | OXISTAT® Lotion
Patient Outcome | b.i.d. | q.d. | Vehicle
Mycological cure | 67% | 64% | 28%
Treatment success | 41% | 34% | 10%

In this study, the improvement and cure rates of the b.i.d.- and q.d.-treated groups did not differ significantly (95% confidence interval) from each other but were statistically (95% confidence interval) superior to the vehicle-treated group.

Cream Formulation: The two pivotal trials for the cream formulation involved 281 evaluable patients (total from both trials) with clinically and microbiologically established tinea pedis.

The combined results of these 2 clinical trials at the 2-week post-treatment follow-up visit are shown in the following table:

 | OXISTAT® Cream
Patient Outcome | b.i.d. | q.d. | Vehicle
Mycological cure | 77% | 79% | 33%
Treatment success | 52% | 43% | 14%

All the improvement and cure rates of the b.i.d.- and q.d.- treated groups did not differ significantly (95% confidence interval) from each other but were statistically (95% confidence interval) superior to the vehicle-treated group.

In addition, pediatric data (95 children ages 10 and under) available with the cream formulation indicate that it is safe and effective for use in children when used as directed. Adverse events were reported in 2 children; 1 child was reported to have reddening of the skin and 1 child was reported to have eczema-like skin alterations.

Tinea (pityriasis) Versicolor: Two pivotal clinical trials of OXISTAT® Cream in tinea (pityriasis) versicolor involved 219 evaluable patients in the q day OXISTAT® and vehicle arms of the trial with clinical and mycological evidence of tinea (pityriasis) versicolor. Patients were treated for 2 weeks with OXISTAT® Cream once daily, or with cream vehicle. The combined results of these clinical trials at the 2-week post-treatment follow-up visit are shown in the following table. These results are based on 207 patients (110 in the OXISTAT® group and 97 in the vehicle group) with efficacy evaluations at this visit.

 | OXISTAT® Cream
Patient Outcome | q.d. | Vehicle
Mycological cure | 88% | 67%
Treatment success | 83% | 62%

Only once a day was shown in both studies to be statistically superior to vehicle for all efficacy parameters at 2 weeks and follow-up.

HOW SUPPLIED

OXISTAT® (oxiconazole nitrate cream) Cream, 1% is supplied in:

30-g tubes (NDC 21695-459-30), and

Store between 15° and 30° C (59° and 86° F).

PharmaDerm®
A division of Nycomed US Inc.
Melville, NY 11747 USA
www.pharmaderm.com

Repackaged by:
Rebel Distributors Corp.
Thousand Oaks, CA 91320

I8358C/IF8358C
R2/09
#178